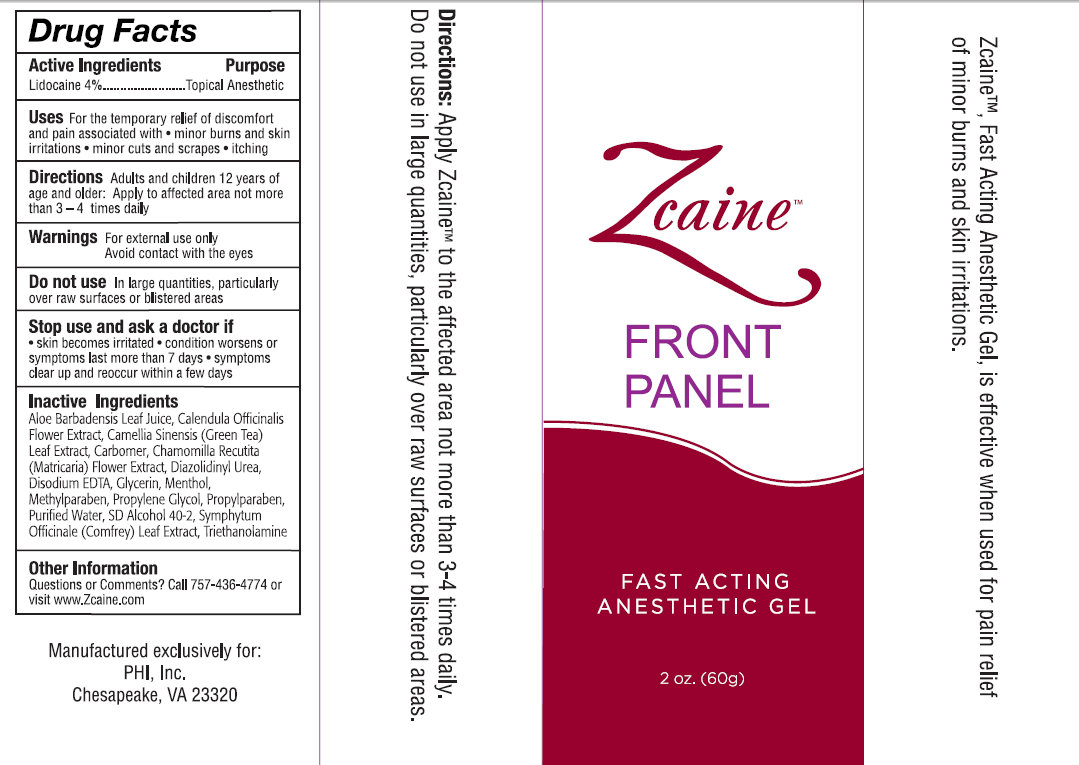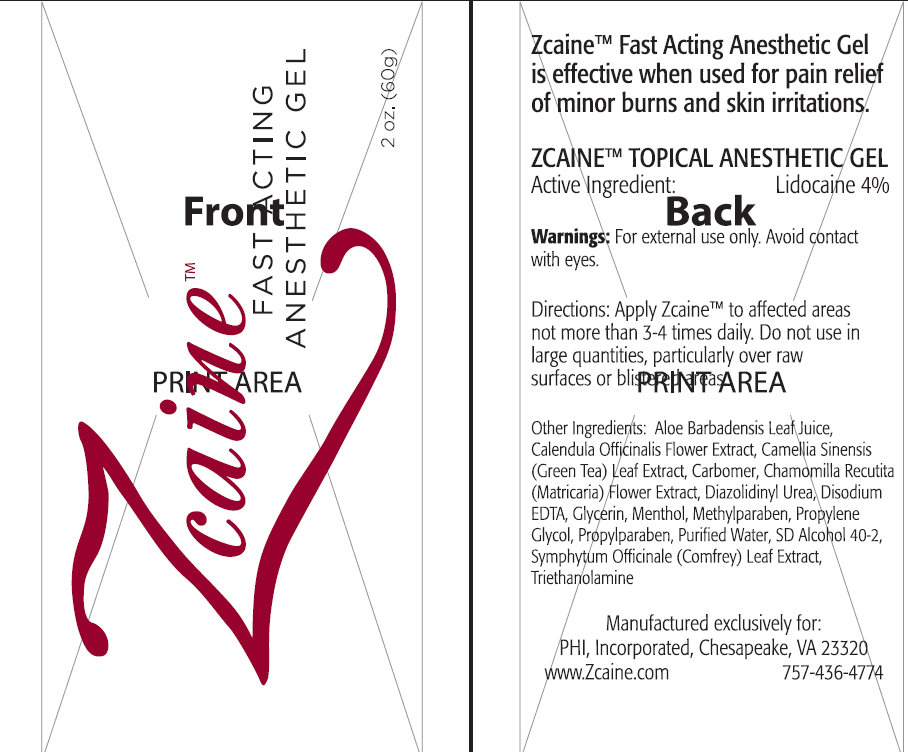 DRUG LABEL: Zcaine Fast Acting Anesthetic
NDC: 27789-911 | Form: GEL
Manufacturer: PHI, Inc
Category: otc | Type: HUMAN OTC DRUG LABEL
Date: 20231109

ACTIVE INGREDIENTS: LIDOCAINE 4 g/100 g
INACTIVE INGREDIENTS: ALOE VERA LEAF; CALENDULA OFFICINALIS FLOWER; GREEN TEA LEAF; CHAMOMILE; DIAZOLIDINYL UREA; EDETATE DISODIUM; GLYCERIN; MENTHOL; METHYLPARABEN; PROPYLENE GLYCOL; PROPYLPARABEN; WATER; ALCOHOL; COMFREY LEAF; TROLAMINE

Zcaine Fast Acting Anesthetic Gel

Active Ingredients

Lidocaine 4%

Purpose

Topical Anesthetic

Uses:

For the temporary relief of discomfort and pain associated with

- minor burns and skin irritations
- minor cuts and scrapes
- itching

Warnings:

For external use only.

Avoid contact with eyes.

In large quantities, particularly over raw surfaces or blistered areas Do not use

Stop use and ask a doctor if

- skin becomes irritated
- condition worsens or symptoms last more than 7 days
- symptoms clear up and reoccur within a few days

Directions

Adults and children 12 years of age or older: Apply to affected area not more than 3 to 4 times daily.

Other Ingredients:

Aloe Barbadensis Leaf Juice, Calendula Officinalis Flower Extract, Camellia Sinensis (Green Tea) Leaf Extract, Carbomer, Chamomilla Recutita (Matricaria) Flower Extract, Diazolidinyl Urea, Disodium EDTA, Glycerin, Menthol, Methylparaben, Propylene Glycol, Propylparaben, Purified Water, SD Alcohol 40-2, Symphytum Officinale (Comfrey) Leaf Extract, Triethanolamine